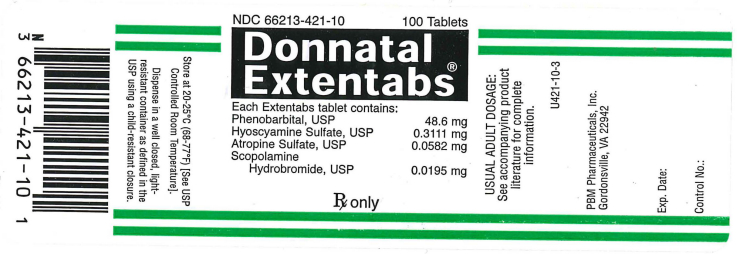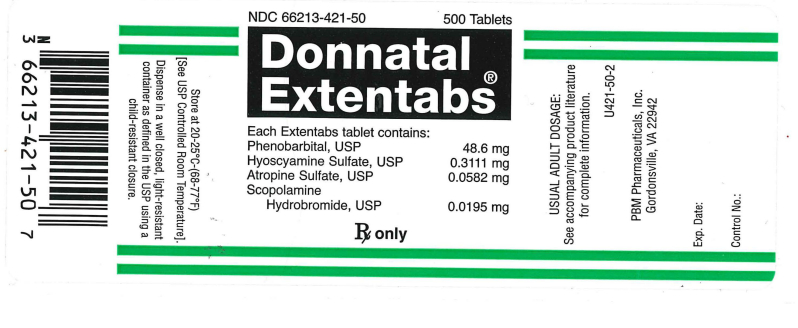 DRUG LABEL: Donnatal Extentabs
NDC: 66213-421 | Form: TABLET, FILM COATED, EXTENDED RELEASE
Manufacturer: PBM Pharmaceuticals, Inc
Category: prescription | Type: HUMAN PRESCRIPTION DRUG LABEL
Date: 20111017

ACTIVE INGREDIENTS: Phenobarbital 48.6 mg/1 1; HYOSCYAMINE SULFATE 0.3111 mg/1 1; ATROPINE SULFATE 0.0582 mg/1 1; SCOPOLAMINE HYDROBROMIDE 0.0195 mg/1 1
INACTIVE INGREDIENTS: ANHYDROUS LACTOSE; CALCIUM SULFATE, UNSPECIFIED; SILICON DIOXIDE; CALCIUM PHOSPHATE, DIBASIC, ANHYDROUS; LACTOSE MONOHYDRATE; MAGNESIUM STEARATE; STEARIC ACID; D&C YELLOW NO. 10; FD&C BLUE NO. 1; HYPROMELLOSE 2208 (4000 MPA.S); POLYDEXTROSE; POLYETHYLENE GLYCOL 2000; TITANIUM DIOXIDE; TRIACETIN

Donnatal Extentabs

Patient Insert

DONNATAL EXTENTABS®

Rx Only

Rev. 06/07

Description:

Each Donnatal Extentabs® tablet contains:
Phenobarbital, USP (3/4 gr.) 48.6 mg
Hyoscyamine Sulfate, USP 0.3111 mg
Atropine Sulfate, USP 0.0582 mg
Scopolamine Hydrobromide, USP .0.0195 mg
Each Donnatal Extentabs® tablet contains the equivalent of three Donnatal® tablets. Extentabs are designed to release the ingredi¬ents gradually to provide effects for up to twelve (12) hours.
In addition, each tablet contains the following inactive ingredients: Anhydrous Lactose, Calcium Sulfate Granular, Colloidal Silicon Dioxide, Dibasic Calcium Phosphate, Lactose Monohydrate, Magnesium Stearate, and Stearic Acid. Film Coating and Polishing Solution contains: D and C Yellow #10 Aluminum Lake, FD and C Blue #1 Aluminum Lake, Hydroxypropyl Methylcellulose, Polydextrose, Polyethylene Glycol, Titanium Dioxide, and Triacetin. The printing ink contains Titanium Dioxide.

ACTIONS:

This drug combination provides natural belladonna alkaloids in a specific, fixed ratio combined with phenobarbital to provide peripheral anticholinergic/antispasmodic action and mild sedation.

INDICATIONS

Based on a review of this drug by the National Academy of Sciences - National Research Council and/or other information, FDA has classified the following indications as “possibly” effective:
For use as adjunctive therapy in the treatment of irritable bowel syndrome (irritable colon, spastic colon, mucous colitis) and acute enterocolitis.
May also be useful as adjunctive therapy in the treatment of duodenal ulcer. IT HAS NOT BEEN SHOWN CONCLUSIVELY WHETHER ANTICHOLINERGIC/ANTISPASMODIC DRUGS AID IN THE HEALING OF A DUODENAL ULCER, DECREASE THE RATE OF RECURRENCES OR PREVENT COMPLICATIONS.

CONTRAINDICATIONS:

Glaucoma, obstructive uropathy (for example, bladder neck obstruction due to prostatic hypertrophy); obstructive disease of the gastrointestinal tract (as in achalasia, pyloroduodenal stenosis, etc.); paralytic ileus, intestinal atony of the elderly or debilitated patient; unstable cardiovascular status in acute hemorrhage; severe ulcerative colitis especially if complicated by toxic megacolon; myasthenia gravis; hiatal hernia associated with reflux esophagitis.
Donnatal Extentabs® is contraindicated in patients with known hypersensitivity to any of the ingredients. Phenobarbital is contraindicated in acute intermittent porphyria and in those patients in whom phenobarbital produces restlessness and/or excitement.

WARNINGS:

In the presence of a high environmental temperature, heat prostration can occur with belladonna alkaloids (fever and heatstroke due to decreased sweating).
Diarrhea may be an early symptom of incomplete intestinal obstruction, especially in patients with ileostomy or colostomy. In this instance treatment with this drug would be inappropriate and possibly harmful.
Donnatal Extentabs® may produce drowsiness or blurred vision. The patient should be warned, should these occur, not to engage in activities requiring mental alertness, such as operating a motor vehicle or other machinery, and not to perform hazardous work.
Phenobarbital may decrease the effect of anticoagulants and necessitate larger doses of the anticoagulant for optimal effect. When phenobarbital is discontinued, the dose of the anticoagulant may have to be decreased.
Phenobarbital may be habit forming and should not be administered to individuals known to be addiction prone or to those with a history of physical and/or psychological dependence upon drugs.
Since barbiturates are metabolized in the liver, they should be used with caution and initial doses should be small in patients with hepatic dysfunction.

PRECAUTIONS:

Use with caution in patients with: autonomic neuropathy, hepatic or renal disease, hyperthyroidism, coronary heart disease, congestive heart failure, cardiac arrhythmias, tachycardia, and hypertension.
Belladonna alkaloids may produce a delay in gastric emptying (antral stasis) which would complicate the management of gastric ulcer.
Theoretically, with overdosage, a curare-like action may occur.

Carcinogenesis, mutagenesis:

Long-term studies in animals have not been performed to evaluate carcinogenic potential.

Pregnancy Category C:

Animal reproduction studies have not been conducted with Donnatal Extentabs®. It is not known whether Donnatal Extentabs® can cause fetal harm when administered to a pregnant woman or can affect reproduction capacity. Donnatal Extentabs® should be given to a pregnant woman only if clearly needed.

Nursing mothers:

It is not known whether this drug is excreted in human milk. Because many drugs are excreted in human milk, caution should be exercised when Donnatal Extentabs® is administered to a nursing mother.

ADVERSE REACTIONS:

Adverse reactions may include xerostomia; urinary hesitancy and retention; blurred vision; tachycardia; palpitation; mydriasis; cycloplegia; increased ocular tension; loss of taste sense; headache; nervousness; drowsiness; weakness; dizziness: insomnia; nausea; vomiting; impotence; suppression of lactation; constipation; bloated feeling; musculoskeletal pain; severe allergic reaction or drug idiosyncrasies, including anaphylaxis, urticaria and other dermal manifestations; and decreased sweating. Acquired hypersensitivity to barbituates consists chiefly in allergic reactions that occur especially in persons who tend to have asthma, urticaria, angioedema and similar conditions. Hypersensitivity reactions in this category include localized swelling, particularly of the eyelids, cheeks, or lips, and erythematous dermatitis. Rarely, exfoliative dermatitis (e.g. Stevens-Johnson syndrome and toxic epidermal necrolysis) may be caused by phenobarbital and can prove fatal. The skin eruption may be associated with fever, delirium, and marked degenerative changes in the liver and other parenchymatous organs. In a few cases, megaloblastic anemia has been associated with the chronic use of phenobarbital. Elderly patients may react with symptoms of excitement, agitation, drowsiness, and other untoward manifestations to even small doses of the drug.
Phenobarbital may produce excitement in some patients, rather than a sedative effect. In patients habituated to barbiturates, abrupt withdrawal may produce delirium or convulsions.

DOSAGE AND ADMINISTRATION:

The dosage of Donnatal Extentabs® should be adjusted to the needs of the individual patient to assure symptomatic control with a minimum of adverse reactions. The usual dose is one tablet every twelve (12) hours. If indicated, one tablet every eight (8) hours may be given.

OVERDOSAGE:

The signs and symptoms of overdose are headache, nausea, vomiting, blurred vision, dilated pupils, hot and dry skin, dizziness, dryness of the mouth, difficulty in swallowing, and CNS stimulation. Treatment should consist of gastric lavage, emetics, and activated charcoal. If indicated, parenteral cholinergic agents such as physostigmine or bethanechol chloride should be added.

HOW SUPPLIED:

Donnatal Extentabs® Tablets are supplied as: film coated green, round, compressed tablets printed “P421” in black ink.
Bottles of 100 tablets
Bottles of 500 tablets
Store at 20-25°C (68-77°F) [See USP Controlled Room Temperature]. Protect from light and moisture.
Dispense in a well-closed, light-resistant container as defined in the USP using a child-resistant closure.
Also available: Donnatal® Tablets in bottles of 100 and 1000 tablets and Donnatal® Elixir in 4 fl oz bottles and 1 pint bottles.

Manufactured For:
PBM Pharmaceuticals, Inc.
Gordonsville, VA 22942
Manufactured By:
West-ward Pharmaceutical Corp.
Eatontown, NJ 07724 Revised June 2007

PACKAGE LABEL

NDC 66213-421-10 100 Tablets
Donnatal Extentabs®
Each Extentabs tablet contains:
Phenbarbital, USP . . . . 48.6 mg
Hyoscyamine Sulfate, USP . . . . . . . 0.3111 mg
Atropine Sulfate, USP . . . . . . 0.0582 mg
Scopolamine Hydrobromide, USP . . . . . . . . . 0.0195 mg
RX only
Usual Adult Usage:
See accompanying product literature for complete information.
U421-10-3
PBM Pharmaceuticals, Inc.
Charlottesville, VA 22902
Exp. Date:
Control No:
Store at 20-25°C (68-77°F) [See USP Controlled Room Temperature].
Dispense in a well closed, light resistant container as defined in the USP using a child-resistant closure.

PACKAGE LABEL

NDC 66213-421-50 500 Tablets
Donnatal Extentabs®
Each Extentabs tablet contains:
Phenbarbital, USP . . . . 48.6 mg
Hyoscyamine Sulfate, USP . . . . . . . 0.3111 mg
Atropine Sulfate, USP . . . . . . 0.0582 mg
Scopolamine Hydrobromide, USP . . . . . . . . . 0.0195 mg
RX only
Usual Adult Usage:
See accompanying product literature for complete information.
U425-50-2
PBM Pharmaceuticals, Inc.
Charlottesville, VA 22902
Exp. Date:
Control No:
Store at 20-25°C (68-77°F) [See USP Controlled Room Temperature].
Dispense in a well closed, light resistant container as defined in the USP using a child-resistant closure.